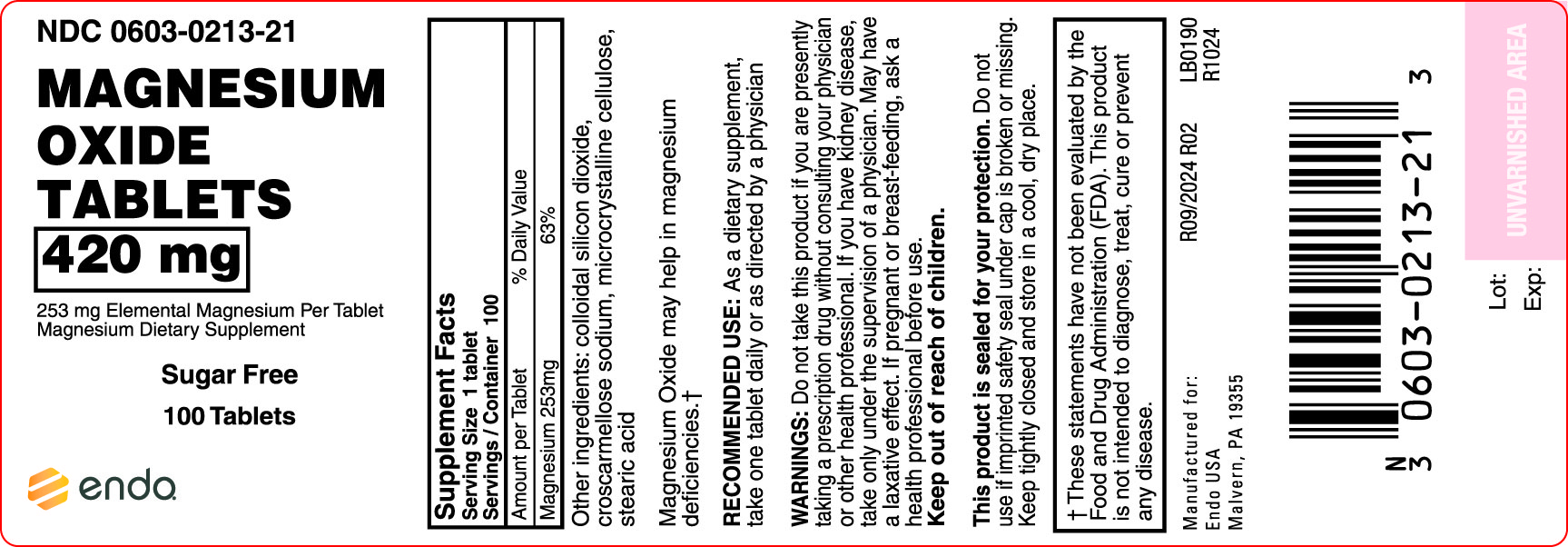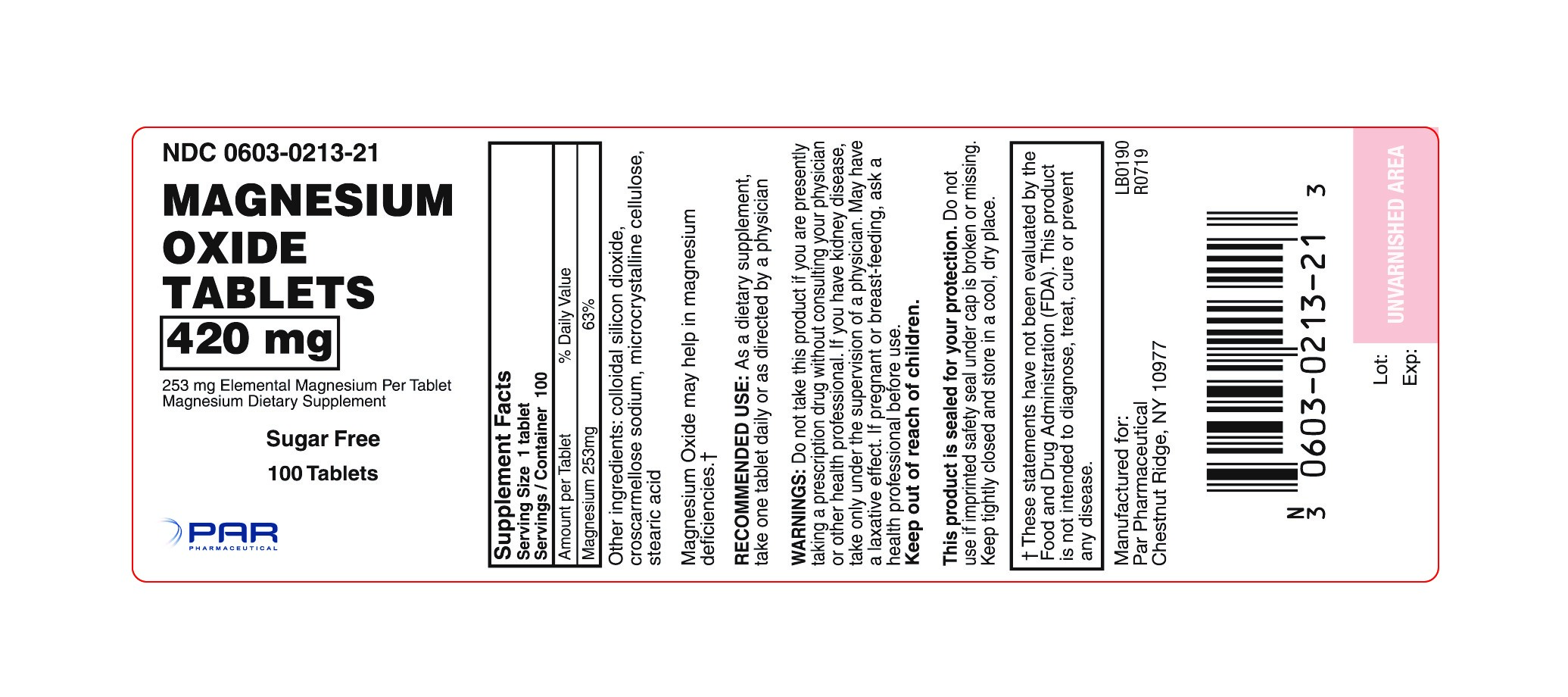 DRUG LABEL: Magnesium Oxide
NDC: 0603-0213 | Form: TABLET
Manufacturer: Endo USA
Category: otc | Type: HUMAN OTC DRUG LABEL
Date: 20201110

ACTIVE INGREDIENTS: MAGNESIUM OXIDE 253 mg/1 1
INACTIVE INGREDIENTS: SILICON DIOXIDE; CROSCARMELLOSE SODIUM; CELLULOSE, MICROCRYSTALLINE; STEARIC ACID

306-Magnesium Oxide 420mg

Active ingredient(s)

Magnesium Oxide

Purpose

Magnesium Oxide may help in magnesium deficiencies †

Use(s)

As a dietary supplement.

Warnings

Do not use

Do not take this product if you are presently taking a prescription drug without consulting your physician or other health care professional. If you have kidney disease, take only under the supervision of a physician. May have a laxative effect.

Pregnancy/Breastfeeding

ask a health professional before use.

Directions

Take one tablet daily or as directed by a physician.

Other information

This product is sealed for your protection. Do not use if imprinted safety seal under cap is broken or missing.

Storage

Keep tightly closed and store in a cool, dry place.

Inactive ingredients

colloidal silicon dioxide, croscarmellose sodium, microcrystalline cellulose, stearic acid.

Principal Display Panel

Magnesium Oxide
†These statements have not been evaluated by The Food and Drug Administration (FDA). This product is not intended to diagnose, treat, cure or prevent any disease. Manufactured for: Qualitest Pharmaceuticals 130 Vintage Drive Huntsville, AL 35811 USA